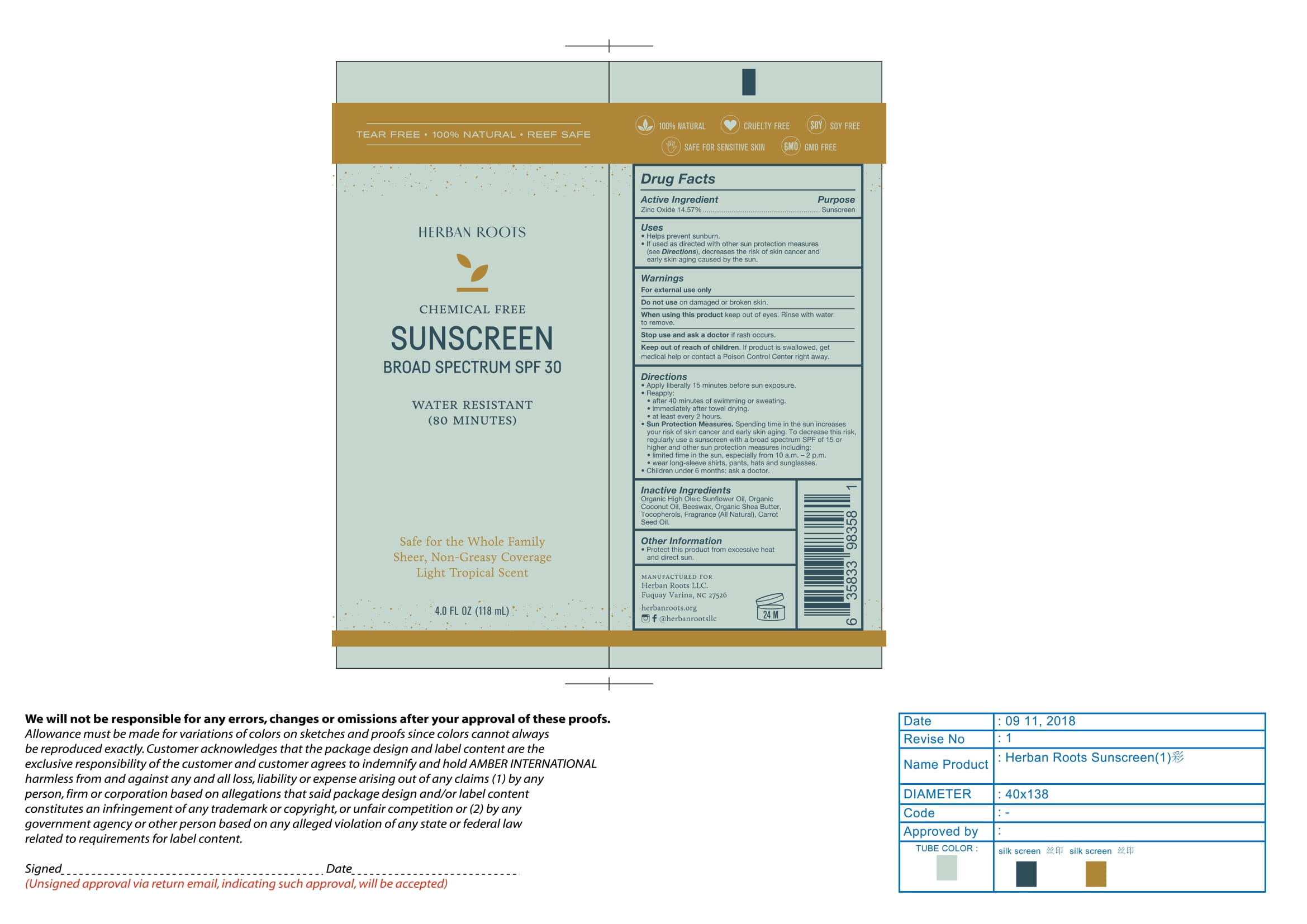 DRUG LABEL: Sunscreen Broad Spectrum SPF 30 Light Tropical Scent
NDC: 56152-0101 | Form: CREAM
Manufacturer: Cosmetic Enterprises Ltd
Category: otc | Type: HUMAN OTC DRUG LABEL
Date: 20251014

ACTIVE INGREDIENTS: ZINC OXIDE 14.57 g/100 mL
INACTIVE INGREDIENTS: YELLOW WAX; SUNFLOWER OIL; COCONUT OIL; TOCOPHEROL; CARROT SEED OIL; SHEA BUTTER

Sunscreen Broad Spectrum SPF 30 Light Tropical Scent

Active ingredient Purpose

Zinc Oxide 14.57% Sunscreen

Uses

- Helps prevent sunburn
- If used as directed with other sun protection measures (see Directions), decreases the risk of skin cancer and early skin aging caused by the sun.

Keep out of reach of children. If product is swallowed, get medical help or contact a Poison Control Center right away.

Stop use and ask a doctorif rash occurs.

Warnings

For External use only

Do not useon damaged or broken skin

When using this productkeep out of eyes. Rinse with water to remove.

Directions

- Apply liberally 15 minutes before sun exposure
- Reapply
- After 40 minutes of swimming or sweating .
- Immediately after towel drying
- at least every 2 hours
- Sun Protection Measures. Spending time in the sun increases your risk of skin cancer and early skin aging. To decrease this risk, regularly use a sunscreen with a broad spectrum SPF of 15 or higher and other sun protection measures:
- limited time in the sun, especially from 10 a.m. - 2 p.m.
- wear long-sleeve shirts, pants, hats and sunglasses.
- Children under 6 months: ask a doctor

Inactive Ingredients

Organic High Oleic Sunflower Oil, Organic Coconut Oil, Beeswax, Organic Shea Butter, Tocopherols, Fragrance (All Natural), Carrot Seed Oil.

Other information

- Protect this product from excessive heat and direct sun

PACKAGE LABEL

Herban Roots

Chemical Free

Sunscreen Broad Spectrum SPF 30

Water resistant (80 minutes)

Safe for the Whole Family

Sheer, Non-Greasy Coverage

Light Tropical Scent

4.0 FL OZ (118 mL)